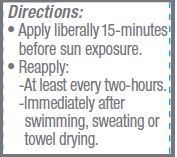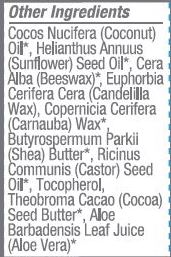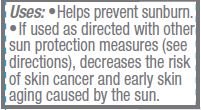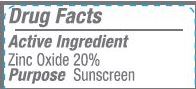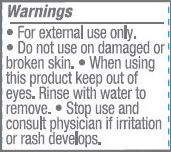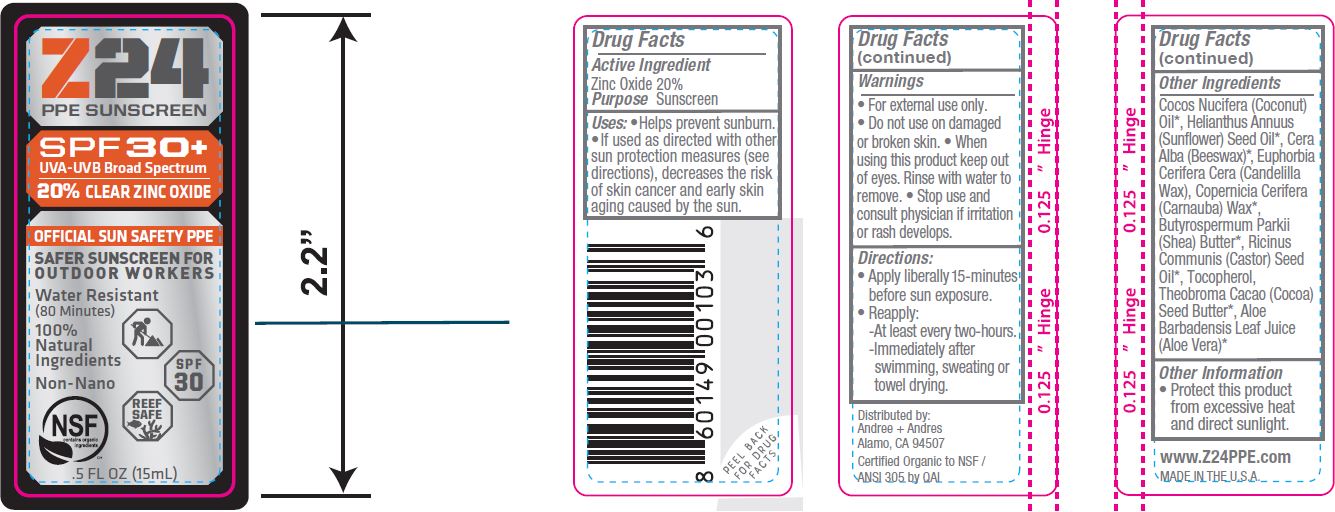 DRUG LABEL: SUNSCREEN
NDC: 62932-192 | Form: STICK
Manufacturer: Private Label Select Ltd CO
Category: otc | Type: HUMAN OTC DRUG LABEL
Date: 20190618

ACTIVE INGREDIENTS: ZINC OXIDE 20 g/100 g
INACTIVE INGREDIENTS: CASTOR OIL; SUNFLOWER OIL; COCONUT OIL; YELLOW WAX; CANDELILLA WAX; SHEA BUTTER; COCOA BUTTER; CARNAUBA WAX; TOCOPHEROL; ALOE VERA LEAF

Z24 SPF 30 Sun Stick